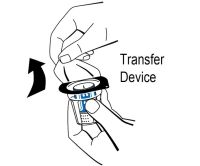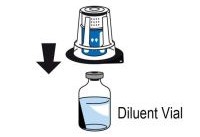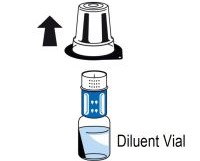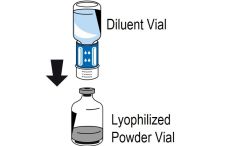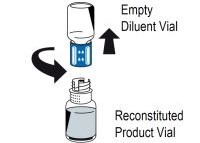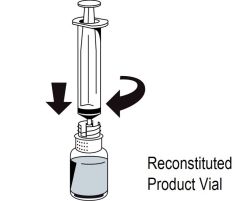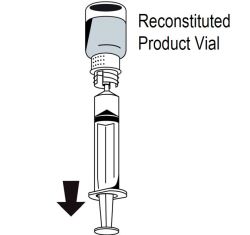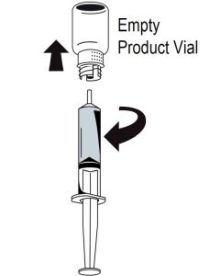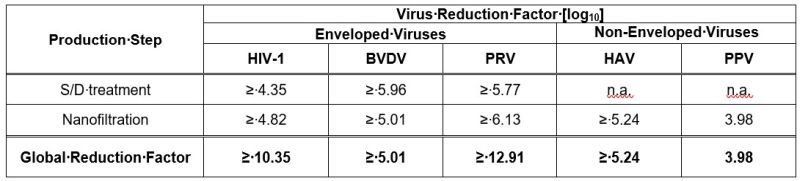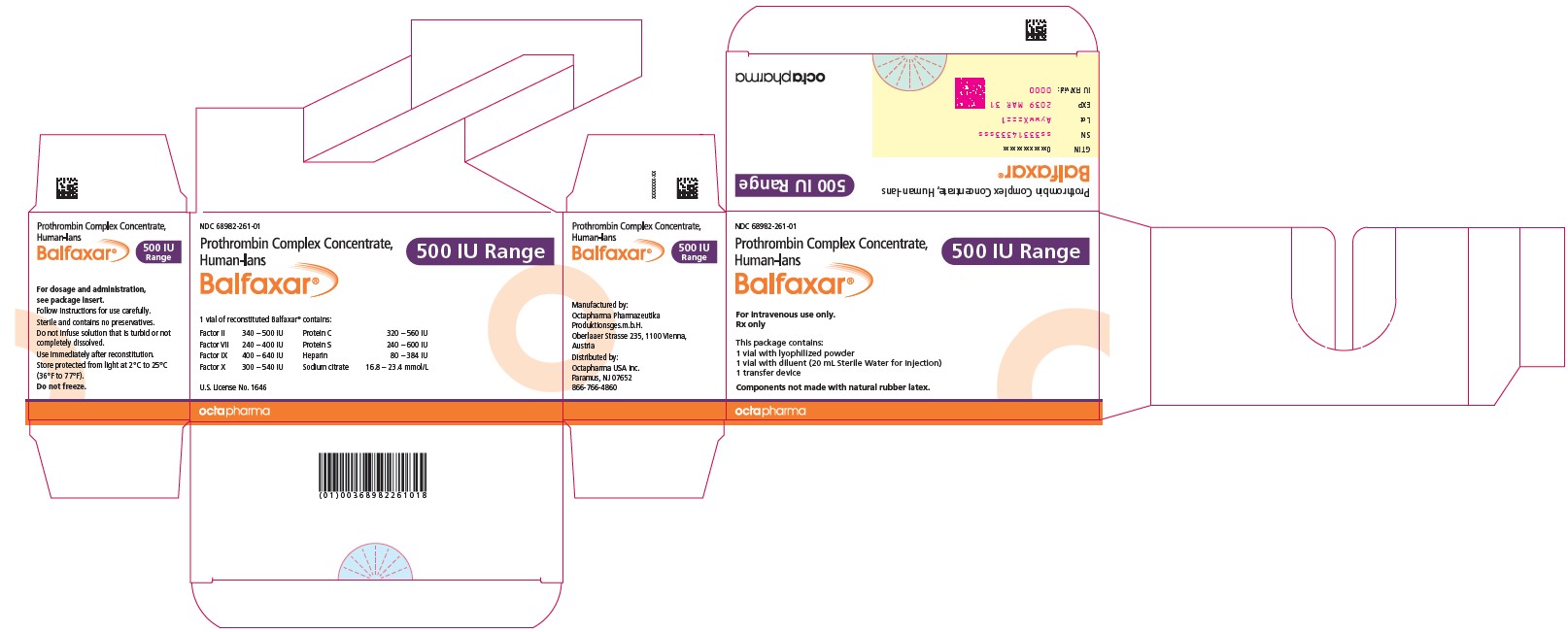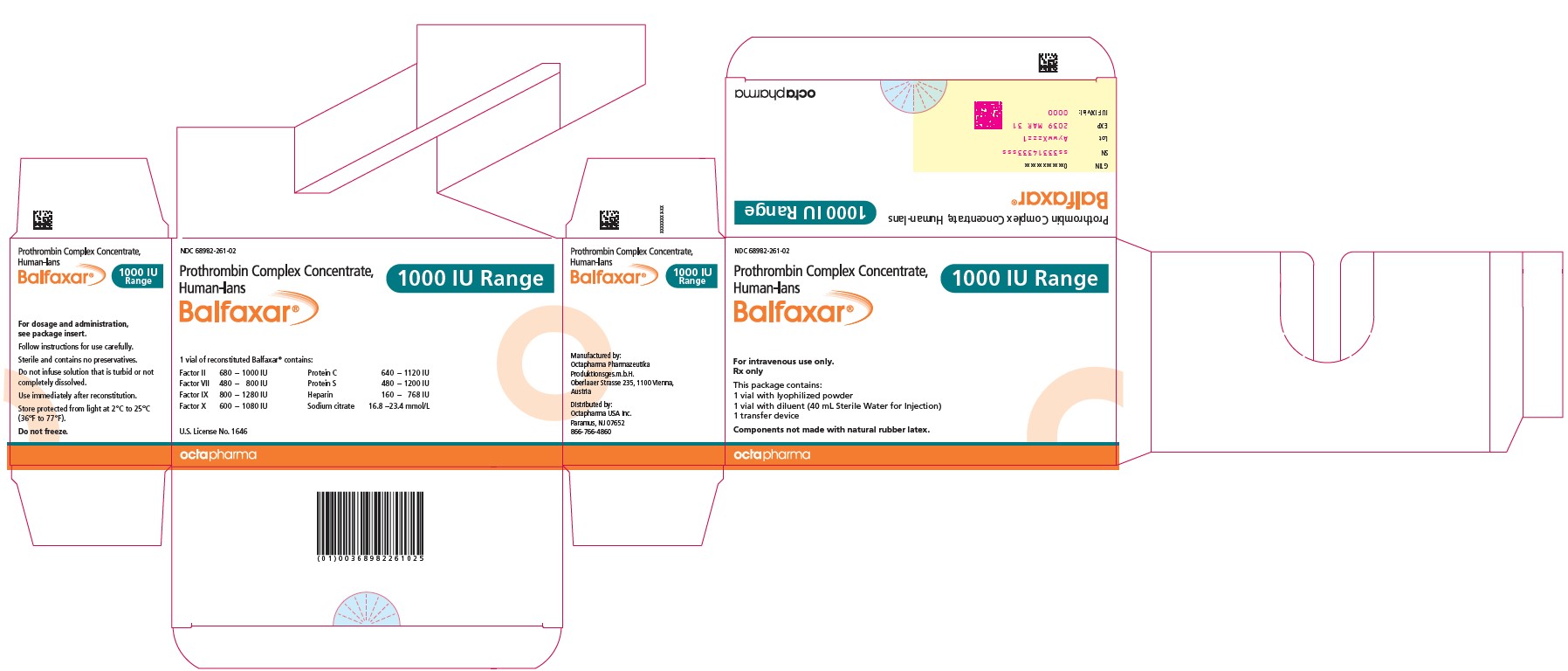 DRUG LABEL: Balfaxar
NDC: 68982-261 | Form: POWDER, FOR SOLUTION
Manufacturer: Octapharma USA Inc
Category: other | Type: PLASMA DERIVATIVE
Date: 20230721

ACTIVE INGREDIENTS: COAGULATION FACTOR IX HUMAN 25.5 [iU]/1 mL; PROTHROMBIN 26 [iU]/1 mL; COAGULATION FACTOR VII HUMAN 16.5 [iU]/1 mL; COAGULATION FACTOR X HUMAN 24 [iU]/1 mL; PROTEIN C 22 [iU]/1 mL; PROTEIN S HUMAN 22 [iU]/1 mL

HIGHLIGHTS OF PRESCRIBING INFORMATION

These highlights do not include all the information needed to use BALFAXAR safely and effectively. See full prescribing information for BALFAXAR.
BALFAXAR (prothrombin complex concentrate, human-lans)
lyophilized powder for solution, for intravenous use
Initial U.S. Approval: 2023

WARNING: ARTERIAL AND VENOUS THROMBOEMBOLIC COMPLICATIONS

See full prescribing information for complete boxed warning .

Patients being treated with Vitamin K antagonists (VKA) therapy have underlying disease states that predispose them to thromboembolic events. Potential benefits of reversing VKA should be weighed against the potential risks of thromboembolic events, especially in patients with the history of a thromboembolic event. Resumption of anticoagulation should be carefully considered as soon as the risk of thromboembolic events outweighs the risk of acute bleeding.

Both fatal and non-fatal arterial and venous thromboembolic complications have been reported with BALFAXAR in clinical trials and post marketing surveillance. Monitor patients receiving BALFAXAR for signs and symptoms of thromboembolic events. (5.2)

BALFAXAR may not be suitable in patients with thromboembolic events in the prior 3 months. (5.2)

1 INDICATIONS AND USAGE

BALFAXAR (prothrombin complex concentrate, human-lans) is a blood coagulation factor replacement product indicated for the urgent reversal of acquired coagulation factor deficiency induced by Vitamin K antagonist (VKA, e.g., warfarin) therapy in adult patients with need for an urgent surgery/invasive procedure. (1)

2 DOSAGE AND ADMINISTRATION

For intravenous use after reconstitution only.

BALFAXAR dosing should be individualized based on the patient’s baseline International Normalized Ratio (INR) value, and body weight. (2.1)

Administer Vitamin K concurrently to patients receiving BALFAXAR to maintain factor levels once the effects of BALFAXAR have diminished. (14)

The safety and effectiveness of repeat dosing have not been established and it is not recommended. (2.1)

Administer reconstituted BALFAXAR at a rate of 0.12 mL/kg/min (~3 units/kg/min) up to a maximum rate of 8.4 mL/min (~210 units/min). (2.3)

Pre-treatment INR | 2-< 4 | 4-6 | > 6
Dose# of BALFAXAR (units† of Factor IX) / kg body weight | 25 | 35 | 50
Maximum dose‡ (units of Factor IX) | Not to exceed 2500 | Not to exceed 3500 | Not to exceed 5000

# Dosing is based on body weight. Dose based on actual potency is stated on the vial, which will vary from 20-32 Factor IX units/mL after reconstitution.

The actual potency for a 500 unit vial ranges from 400-640 units/vial. The actual potency for a 1000 unit vial ranges from 800-1280 units/vial.

† Units refer to International Units.

‡ Dose is based on body weight up to but not exceeding 100 kg. For patients weighing more than 100 kg, maximum dose should not be exceeded. (2.2)

3 DOSAGE FORMS AND STRENGTHS

BALFAXAR is available as a white to ice-blue lyophilized powder for reconstitution for intravenous use in a single-dose vial, provided in a nominal strength of 500 Factor IX units in 20 mL reconstitution volume and 1000 Factor IX units in 40 mL reconstitution volume per vial. BALFAXAR contains the coagulation factors II, VII, IX, and X and antithrombotic Proteins C and S. (3)

4 CONTRAINDICATIONS

Known anaphylactic or severe systemic reactions to BALFAXAR or any of the components of the product. (4)

Known allergy to heparin or history of heparin-induced thrombocytopenia (HIT). (4)

IgA deficient patients with known antibodies against IgA. (4)

5 WARNINGS AND PRECAUTIONS

Discontinue infusion if allergic or anaphylactic-type reactions occur. Initiate appropriate treatment. (5.1)

Arterial and venous thromboembolic complications have been reported in patients receiving BALFAXAR. Monitor patients receiving BALFAXAR for signs and symptoms of thromboembolic events. (5.2)

BALFAXAR is made from human plasma; therefore, may carry the risk of transmitting infectious agents, e.g., viruses, the variant Creutzfeldt-Jakob disease (vCJD) agent, and theoretically, the Creutzfeldt-Jakob disease (CJD) agent. (5.3)

6 ADVERSE REACTIONS

The most common adverse reactions observed in ≥ 3% of subjects were procedural pain, wound complications, asthenia, anemia, dysuria, procedural vomiting and catheter site related reaction. (6)

To report SUSPECTED ADVERSE REACTIONS, contact Octapharma USA Inc. at 1-866-766-4860 or FDA at 1-800-FDA-1088 or www.fda.gov/medwatch.

_________________________________________________________________________________________________________________________

FULL PRESCRIBING INFORMATION

WARNING: ARTERIAL AND VENOUS THROMBOEMBOLIC COMPLICATIONS

Patients being treated with Vitamin K antagonist (VKA) therapy have underlying disease states that predispose them to thromboembolic events. Potential benefits of reversing VKA should be weighed against the potential risks of thromboembolic events, especially in patients with the history of a thromboembolic event. Resumption of anticoagulation should be carefully considered as soon as the risk of thromboembolic events outweighs the risk of acute bleeding.

- Both fatal and non-fatal arterial and venous thromboembolic complications have been reported with BALFAXAR in clinical trials and post marketing surveillance. Monitor patients receiving BALFAXAR for signs and symptoms of thromboembolic events. [see Warnings and Precautions (5.2)].

- BALFAXAR may not be suitable in patients with thromboembolic events in the prior 3 months. [see Warnings and Precautions (5.2)].

1 INDICATIONS AND USAGE

BALFAXAR (prothrombin complex concentrate, human-lans) is a blood coagulation factor replacement product indicated for the urgent reversal of acquired coagulation factor deficiency induced by Vitamin K antagonist (VKA, e.g., warfarin) therapy in adult patients with need for an urgent surgery/invasive procedure.

2 DOSAGE AND ADMINISTRATION

For intravenous use after reconstitution only .

2.1 Dosage

- Measurement of INR prior to treatment and close to the time of dosing is important because coagulation factors may be unstable in patients with need for an urgent surgery and other invasive procedures.
- Individualize BALFAXAR dosing based on the patient’s current pre-dose International Normalized Ratio (INR) value, and body weight (see Table 1).
- The actual potency per vial of Factor IX is stated on the carton. The potencies of Factors II, VII, IX and X, Proteins C and S are indicated as ranges.
- Administer Vitamin K concurrently to patients receiving BALFAXAR. Vitamin K is administered to maintain Vitamin K-dependent clotting factor levels once the effects of BALFAXAR have diminished.
- The safety and effectiveness of repeat dosing have not been established and it is not recommended.
- Dose ranging within pre-treatment INR groups has not been studied in randomized clinical trials of BALFAXAR.

Table 1 Dosage Required for Reversal of VKA Anticoagulation in Patients with Need for an Urgent Surgery/Invasive Procedure

Pre-treatment INR | 2-< 4 | 4-6 | > 6
Dose* of BALFAXAR (units † of Factor IX) / kg body weight | 25 | 35 | 50
Maximum dose ‡ (units of Factor IX) | Not to exceed 2500 | Not to exceed 3500 | Not to exceed 5000

* Dosing is based on body weight. Dose based on actual potency is stated on the vial, which will vary from 20-32 Factor IX units/mL after reconstitution. The actual potency for a 500 unit vial ranges from 400-640 units/vial. The actual potency for a 1000 unit vial ranges from 800-1280 units/vial.

† Units refer to International Units.

‡ Dose is based on body weight up to but not exceeding 100 kg. For patients weighing more than 100 kg, maximum dose should not be exceeded.

Example dosing calculation for 80 kg patient:

For example, an 80 kg patient with a baseline of INR of 5.0, the dose would be 2,800 Factor IX units of BALFAXAR, calculated as follows based on INR range of 4-6, see Table 1 :

35 units of Factor IX/kg x 80 kg = 2,800 units of Factor IX required*

* For a vial with an actual potency of 30 units/mL Factor IX, 93 mL would be given (2,800 U/30 U per mL = 93 mL).

Monitor INR and clinical response during and after treatment. In clinical trials, BALFAXAR decreased the INR to ≤1.5 within 30 minutes in most subjects. The relationship between this or other INR values and clinical hemostasis in patients has not been established [see Clinical Studies (14)] .

2.2 Preparation and Reconstitution

BALFAXAR is provided with a transfer device (Nextaro ®) for reconstitution of the lyophilized powder in diluent (sterile Water for Injection (sWFI)).

BALFAXAR is for single dose only. Do not re-use any of the components.

Inspect all components for physical integrity prior to use. Do not use products or components that appear damaged or broken.

Reconstitute BALFAXAR using aseptic technique for the procedure described below.

The product reconstitutes quickly (1 to 5 minutes) at room temperature (20°C to 25°C; 68°F to 77°F). As BALFAXAR contains no preservatives, the solution should be administered immediately after reconstitution, or within 8 hours, provided sterility is maintained. The reconstituted solution can be stored for up to 8 hours at room temperature (20°C to 25°C; 68°F to 77°F).

Instructions for Reconstitution:

Figure 1

1. Ensure that the lyophilized powder and diluent vials are at room temperature (20°C to 25°C, 68°F to 77°F). This temperature should be maintained during reconstitution.
2. Remove the flip caps from the lyophilized powder and diluent vials and disinfect the rubber stoppers with an alcohol swab and allow to dry.
3. Open the transfer device package by peeling off the lid (Figure 1). To maintain sterility, do not remove the transfer device from the blister package and do not touch the spike.

Figure 2

4. Place the diluent vial on an even, clean surface and hold it firmly. Without removing the blister package, place the blue part of the transfer device on top of the diluent vial and press straight and firmly down until it snaps into place (Figure 2). Do not twist while attaching.

Figure 3

5. While holding onto the diluent vial, carefully remove the blister package from the transfer device by pulling vertically upwards. Make sure to leave the transfer device attached firmly to the diluent vial (Figure 3).

Figure 4

6. Place the lyophilized powder vial on an even, clean surface and hold it firmly. Take the diluent vial with the attached transfer device and turn it upside down. Place the white part of the transfer device connector on top of the powder vial and press firmly down until it snaps into place (Figure 4). Do not twist while attaching. The diluent will flow automatically into the powder vial.
Note: The transfer device must be attached to the diluent vial first and then to the lyophilized powder vial. Otherwise, loss of vacuum occurs, and transfer of the diluent does not take place. If diluent is not completely transferred to the lyophilized powder vial during this process, contact your Octapharma representative.

Figure 5

7. With both vials still attached, gently swirl the product vial until the product is fully dissolved. To avoid foam formation, do not shake the vial. BALFAXAR dissolves quickly at room temperature (20°C to 25°C; 68°F to 77°F) and is a clear solution that may be colorless to slightly blue. Unscrew the transfer device counterclockwise into two parts (Figure 5). Do not touch the luer lock connector.
8. Dispose of the empty diluent vial together with the blue part of the transfer device.

Reconstituted products should be inspected visually for particulate matter. Do not use solutions that are cloudy or have deposits.

If the lyophilized powder fails to dissolve completely or an aggregate is formed, do not use the preparation.

After reconstitution, administration should begin promptly or within 8 hours, provided sterility is maintained.

If the same patient is to receive more than one vial, you may pool the contents of multiple vials, provided sterility is maintained. Use a separate unused transfer device for the reconstitution of each product vial.

2.3 Administration

BALFAXAR is for intravenous use after reconstitution only.

Do not mix with other medicinal products; administer through a separate infusion line. The infusion line may be flushed with normal saline before and after administration of BALFAXAR.

Instructions for Infusion:

Figure 6

1. Attach a syringe to the luer lock outlet on the white part of the transfer device (Figure 6).

Figure 7

2. Turn the vial upside down and draw the solution into the syringe (Figure 7).

Figure 8

3. Once the solution has been transferred, firmly hold the barrel of the syringe (keeping the syringe plunger facing down) and remove the syringe from the transfer device (Figure 8).
4. Dispose of the white part of the transfer device together with the empty vial.
5.Attach a suitable administration set to the luer adapter of the syringe.
6.Disinfect the intended injection site appropriately.
7.Administer by intravenous infusion at a rate of 0.12 mL/kg/min (~3 units/kg/min), up to a maximum rate of 8.4 mL/min (~210 units/min). No blood should enter the syringe due to the risk of fibrin clot formation.

Any unused product or waste material should be disposed of immediately in accordance with local requirements.

3 DOSAGE FORMS AND STRENGTHS

BALFAXAR is a sterile, white to ice-blue lyophilized powder for reconstitution for intravenous use. It is provided in a single-dose vial with a nominal strength of 500 Factor IX units in 20 mL reconstitution volume and 1000 Factor IX units in 40 mL reconstitution volume per vial. BALFAXAR contains the coagulation factors II, VII, IX, and X and antithrombotic Proteins C and S.

4 CONTRAINDICATIONS

- Known anaphylactic or severe systemic reactions to BALFAXAR or any of the components of the product. For a complete listing of ingredients, [ see Description (11) ].
- Known allergy to heparin or history of heparin-induced thrombocytopenia (HIT).
- IgA deficient patients with known antibodies against IgA.

5 WARNINGS AND PRECAUTIONS

5.1 Hypersensitivity Reactions

If severe allergic or anaphylactic-type reactions occur, immediately discontinue administration of BALFAXAR and initiate appropriate treatment. Therapeutic measures depend on the type and severity of the undesirable effect.

5.2 Thromboembolic Risk/Complications

There is a risk of thrombosis or disseminated intravascular coagulation when patients with acquired deficiency are treated with human prothrombin complex. [ 1 ] Patients given human prothrombin complex should be observed closely for signs or symptoms of disseminated intravascular coagulation or thrombosis. Because of the risk of thromboembolic complications, monitoring of signs and symptoms should be exercised when administering human prothrombin complex to patients with a history of coronary heart disease, patients with liver disease, or to patients at risk of thromboembolic events or disseminated intravascular coagulation. The potential benefit of treatment should be weighed against the risk of complications. BALFAXAR may not be suitable in patients with thrombotic or thromboembolic events in the prior 3 months, as it has not been studied in these patients. Resumption of anticoagulation should be carefully considered following administration of BALFAXAR and vitamin K once the risk of thromboembolic events outweighs the risk of bleeding.

5.3 Transmissible Infectious Agents

Standard measures to prevent infections resulting from the use of medicinal products prepared from human blood or plasma include selection of donors, screening of individual donations and plasma pools for specific markers of infection and the inclusion of effective manufacturing steps for the inactivation/removal of viruses.

Despite this, when medicinal products prepared from human blood or plasma are administered, the possibility of transmitting infectious agents e.g., viruses, the vCJD agent, and theoretically, CJD agent, cannot be completely eliminated. This also applies to unknown or emerging viruses and other pathogens.

The measures taken are considered effective for enveloped viruses such as human immunodeficiency virus (HIV), hepatitis B virus (HBV) and hepatitis C virus (HCV). The measures taken may be of limited value against non-enveloped viruses such as hepatitis A virus (HAV) and human parvovirus B19 (B19V).

B19V infections may be serious for pregnant women (fetal infection) and for individuals with immunodeficiency or increased erythropoiesis, e.g., hemolytic anemia.

All suspected infections thought by a physician to have been possibly transmitted by this product should be reported by the physician or other healthcare provider to Octapharma USA Inc. at 1-866-766-4860.

6 ADVERSE REACTIONS

6.1 Clinical Trials Experience

Because clinical trials are conducted under widely varying conditions, adverse reaction rates observed in the clinical trials of a drug cannot be directly compared to rates in the clinical trials of another drug and may not reflect the rates observed in practice.

In a prospective, randomized, controlled, double-blind, multicenter non-inferiority trial, 208 subjects who required reversal of vitamin K antagonist induced anticoagulation due to the need for urgent surgery were enrolled; 105 received BALFAXAR and 103 Kcentra. Subjects ranged in age from 31 years to 92 years. Adverse reactions for BALFAXAR and the comparator are described below.

Adverse Reactions

The most common adverse reactions observed in ≥ 3% subjects receiving BALFAXAR were procedural pain, wound complications, asthenia, anemia, dysuria, procedural vomiting and catheter site related reaction.

In the post-surgical setting, serious adverse reactions in BALFAXAR treatment arm included cerebral infarction, and pulmonary embolism as well as hemorrhage, acute respiratory failure, shock, subdural hemorrhage. One subject experienced one serious adverse reaction, unstable angina assessed as related to BALFAXAR.

Adverse reactions are summarized for BALFAXAR and Kcentra in the following table:

Table 2 Adverse Reactions Reported in More Than 3% Subjects Following BALFAXAR or Kcentra Administration

System Organ Class Preferred Term | BALFAXAR Subjects (N=105) n (%) | Kcentra Subjects (N=103) n (%)
Blood and lymphatic system disorders
Anemia | 6 (5.7%) | 6 (5.8%)
Gastrointestinal disorders
Abdominal pain | 3 (2.9%) | 5 (4.9%)
General disorders and administration site conditions
Asthenia | 13 (12.4%) | 18 (17.5%)
Catheter site related reaction | 4 (3.8%) | 2 (1.9%)
Injury, poisoning and procedural complications
Postoperative wound complication | 15 (14.3%) | 15 (14.6%)
Procedural pain | 50 (47.6%) | 50 (48.5%)
Procedural vomiting | 4 (3.8%) | 0
Suture related complication | 2 (1.9%) | 4 (3.9%)
Investigations
Blood pressure increased | 0 | 5 (4.9%)
Body temperature increased | 0 | 4 (3.9%)
Renal and urinary disorders
Dysuria | 5 (4.8%) | 2 (1.9%)

Deaths

There were a total of four deaths (3.8%) in the BALFAXAR group between 22 and 45 days post surgery, with one (1%) additional death occurring on day 47 just after completion of the study reporting period and one (1%) death in the Kcentra group 10 days after treatment. No deaths were considered to be related to study treatment.

Thromboembolic Events

There were three subjects (2.9%) with BALFAXAR who experienced four thromboembolic events in the randomized controlled trial in urgent surgery; cerebral infarction, pulmonary embolism, unstable angina and myocardial ischemia. The number of thromboembolic adverse reactions assessed as at least possibly related to study treatment was one (1%) with BALFAXAR (unstable angina). There were no thromboembolic events observed in the Kcentra treatment arm.

The following serious adverse reactions are described below and/or elsewhere in the labeling:

- Hypersensitivity Reactions [ see Warnings and Precautions (5.1) ]
- Arterial and venous thromboembolic complications [ see Boxed Warning and Warning s and Precautions (5.2) ]
- Possible Transmission of Infectious Agents [ see Warnings and Precautions (5.3) ]

6.2 Postmarketing Experience

Because post-marketing reporting of adverse reactions is voluntary and from a population of uncertain size, it is not always possible to reliably estimate the frequency of these reactions or establish a causal relationship to product exposure.

The following adverse reactions have been reported during postmarketing use of BALFAXAR outside the US since 2003:

Table 3 Adverse Reactions Reported During Post-Marketing Use of BALFAXAR

Immune system disorders
Anaphylactic shock, anaphylactic reaction, anaphylactoid reaction, hypersensitivity reaction

Nervous system disorders
Cerebrovascular accident, headache, paresthesia, tremor

Cardiac disorders
Bradycardia, tachycardia, cardiac arrest

Vascular disorders
Thromboembolic events, circulatory collapse, hypotension, hypertension

Respiratory, thoracic and mediastinal disorders
Dyspnea, respiratory failure

Gastrointestinal disorders
Nausea

Skin and subcutaneous tissue disorders
Urticaria, rash, pruritus

General disorders and administration site conditions
Fever, chills

To report SUSPECTED ADVERSE REACTIONS, contact Octapharma USA Inc. at 1-866-766-4860 or FDA at 1-800-FDA-1088 or www.fda.gov/medwatch.

8 USE IN SPECIFIC POPULATIONS

8.1 Pregnancy

Risk Summary

There are no data with BALFAXAR use in pregnancy to inform on drug-associated risk. Animal reproduction studies have not been conducted with BALFAXAR. It is not known whether BALFAXAR can cause fetal harm when administered to a pregnant woman or can affect reproduction capacity. In the U.S. general population, the estimated background risk of major birth defects and miscarriage in clinically recognized pregnancies is 2-4% and 15-20%, respectively.

8.2 Lactation

Risk Summary

There is no information regarding the excretion of BALFAXAR in human milk, the effect on the breastfed infant, or the effects on milk production. The developmental and health benefits of breastfeeding should be considered along with the mother’s clinical need for BALFAXAR and any potential adverse effects on the breastfed child from BALFAXAR or from the underlying maternal condition.

8.4 Pediatric Use

The efficacy and safety of BALFAXAR have not been evaluated in pediatric patients.

8.5 Geriatric Use

Of the total number of subjects (105) with need for an urgent surgery/invasive procedure treated with BALFAXAR to reverse VKA anticoagulation, 59% were 65 years old or greater and 20% were 75 years old or greater. There is no evidence to suggest that BALFAXAR use in the geriatric population is associated with differences in safety or effectiveness.

11 DESCRIPTION

BALFAXAR is a human plasma-derived, purified, virus inactivated and nanofiltered non-activated Prothrombin Complex Concentrate (PCC) containing the coagulation factors II, VII, IX, and X and antithrombotic Proteins C and S. BALFAXAR is supplied as a lyophilized powder for reconstitution for intravenous use. The actual potency printed on the vial label represents the potency of Factor IX. BALFAXAR is sterile, endotoxin-free, and does not contain preservatives. No albumin is added as a stabilizer, and the excipients are heparin and sodium citrate. The diluent for reconstitution of the lyophilized powder is sterile Water for Injection.

The composition of BALFAXAR is as follows:

Component | Potency Range for 500 IU vial | Potency Range for 1000 IU vial
Human Coagulation Factor II | 340-500 IU | 680-1000 IU
Human Coagulation Factor VII | 240-400 IU | 480-800 IU
Human Coagulation Factor IX | 400-640 IU | 800-1280 IU
Human Coagulation Factor X | 300-540 IU | 600-1080 IU
Protein C | 320-560 IU | 640-1120 IU
Protein S | 240-600 IU | 480-1200 IU
Heparin | 80-384 IU | 160-768 IU
Sodium Citrate | 16.8-23.4 mmol/L | 16.8-23.4 mmol/L

All human plasma used in the manufacture of BALFAXAR is obtained from U.S. donors, collected in FDA-approved blood and plasma establishments, and tested by FDA-licensed serological tests for viral markers (Hepatitis B surface antigen (HBsAg), antibodies to HIV-1/2 and HCV). The plasma is tested with Nucleic Acid Testing (NAT) for HCV, HIV-1, HAV, and HBV, and found to be non-reactive (negative), and the plasma is also tested by NAT for B19V to exclude donations with high titers. The limit for the titer of B19V DNA in the manufacturing pool is set not to exceed 10 ^4 IU/mL. Only plasma that passed virus screening is used for production.

The BALFAXAR manufacturing process has the capability to clear viruses by a solvent/detergent (S/D) virus inactivation step and a virus removal nanofiltration step. The mean cumulative virus reduction factors of these steps are summarized in Table 4 .

Table 4 Virus Reduction During BALFAXAR Manufacturing

n.a.: not applicable

BVDV: Bovine Viral Diarrhea Virus, model for HCV

PRV: Pseudorabies Virus, model for large enveloped DNA viruses, e.g., HBV

PPV: Porcine Parvovirus, model for B19V

12 CLINICAL PHARMACOLOGY

12.1 Mechanism of Action

The administration of BALFAXAR provides a rapid increase in plasma levels of the vitamin K-dependent coagulation factors (FII, FVII, FIX, FX) and antithrombotic proteins C and S. Together they are referred to/known as the prothrombin complex. [ 2 ; 3 ] BALFAXAR can temporarily correct the coagulation defect of patients with deficiency of one or several of these factors.

12.2 Pharmacodynamics

In the randomized controlled trial in urgent surgery, the INR was determined at varying time points after the end of infusion. The median INR was 3.0 prior to the infusion and dropped to a median value of 1.30 by the 30-minute time point after the end of infusion. After 24 hours it was 1.25 in the BALFAXAR group (see Table 5).

The relationship between these or other INR values and clinical hemostasis in patients has not been established [see Clinical Studies (14)].

Table 5 Median INR (Min-Max) After End of Infusion in Urgent Surgery RCT

Treatment | Baseline | 30 min | 2 hr | 4 hr | 12 hr | 24 hr
BALFAXAR (N=105) | 3.05 (2.0 - 21.1) | 1.30 (1.0 – 3.1) | 1.28 (1.0 - 2.5) | 1.30 (1.0 - 2.0) | 1.30 (0.9 - 2.7) | 1.25 (0.8 - 3.4)

12.3 Pharmacokinetics

Since BALFAXAR is given intravenously, bioavailability is proportional to the dose administered. BALFAXAR is distributed, metabolized, and excreted in the same manner as the endogenous proteins (see Table 6).

Table 6 Pharmacokinetic Parameters and Recovery of Coagulation Factors, Protein C and Protein S

Parameter | FII | FVII | FIX | FX | Protein C | Protein S
C max (%) | 62.42/1.33(37.00-118.00) | 30.58/1.55(13.00-81.00) | 57.57/1.55(27.00-130.00) | 51.03/1.41(30.00-120.00) | 59.95/1.35(38.00-109.00) | 63.20/1.39(30.00-115.00)
C max,norm (%/IU/kg) | 2.38/1.23(1.38-2.96) | 1.16/1.51(0.48-2.11) | 2.19/1.65(0.84-4.71) | 1.94/1.26(1.08-2.74) | 2.28/1.31(1.17-3.45) | 2.41/1.41(0.90-3.95)
Incremental Recovery** (%/IU/kg) | 1.73/1.33(0.81-2.42) | 0.68/1.88(0.11-1.62) | 1.17/1.83(0.26-2.52) | 1.47/1.34(0.73-2.38) | 1.25/0.54*(0.00-2.22) | 1.47/1.52(0.59-2.35)
Absolute Recovery*** (%) | 75.70/1.34(32.65-116.98) | 29.64/1.90(4.45-78.35) | 51.36/1.82(13.54-115.58) | 64.39/1.37(29.68-114.8) | 54.95/24.60*(0.00-107.04) | 64.26/1.55(23.74-113.66)
t max | 0.17(0.17-3.00) | 0.17(0.17-1.00) | 0.50(0.17-3.00) | 0.17(0.17-3.00) | 0.17(0.00-3.00) | 0.17(0.17-3.00)

Note: Values reported as geometric mean/geometric SDs (range), except for t max which is reported as median (min-max)

*Mean values SD (due to zero values, the geometric mean could not be calculated)

**The incremental recovery is defined as the rise in the plasma concentrations (%) achieved with 1 IU BALFAXAR/kg BW.

***The absolute recovery is defined as the rise in the plasma concentrations (%) achieved by the dose.

13 NONCLINICAL TOXICOLOGY

13.1 Carcinogenesis, Mutagenesis, Impairment of Fertility

Long-term studies in animals to evaluate the carcinogenic potential of BALFAXAR or studies to determine the effects of BALFAXAR on genotoxicity or fertility have not been performed.

14 CLINICAL STUDIES

The efficacy of BALFAXAR was assessed in a randomized, double-blind, multicenter study in comparison to Kcentra, for the reversal of vitamin K antagonist induced anticoagulation in patients needing urgent surgery. A total of 208 subjects with acquired coagulation factor deficiency due to oral Vitamin K antagonist therapy were randomized to a single dose of BALFAXAR (n=105) or Kcentra (n=103). The doses of BALFAXAR and Kcentra based on the nominal Factor IX content (25 units/kg, 35 units/kg, or 50 units/kg) were calculated according to the patient’s baseline INR (2-< 4, 4-6, >6, respectively). The observation period lasted for 45 days post-surgery. The primary endpoint was hemostatic efficacy rating at the end of the surgery assessed by the Independent Endpoint Adjudication Board (IEAB). The study was stopped early due to statistically significant efficacy results at the pre-specified interim analysis, where 94.6% (88/93) of the subjects in the BALFAXAR group and 93.5% (86/92) of the subjects in the Kcentra group achieved effective hemostasis (Table7). The non-inferiority analysis for the proportion difference (98% CI) of 1.1% (-9.2%, 11.5%) was statistically significant (p<0.001) indicating that BALFAXAR was non-inferior to Kcentra. The lower bound of the CI was above the pre-specified noninferiority margin of -15%, indicating that BALFAXAR was non-inferior to Kcentra. At the conclusion of the study, the updated proportions of subjects with effective hemostasis were 94.3% (99/105) in the BALFAXAR group and 94.2% (97/103) in the Kcentra group (Table 7), resulting in a difference (95% CI) of 0.1% (-8.0%, 8.2%).

Table 7 Rating of Hemostatic Efficacy in Urgent Surgery RCT

Effective hemostasis | No. (%) of subjects |  | Proportion difference
 | BALFAXAR | Kcentra | BALFAXAR vs. Kcentra
Interim analysis | 88/93 (94.6%) | 86/92 (93.5%) | 1.1%, 98% CI: (-9.2%, 11.5%)*
Final analysis** | 99/105 (94.3%) | 97/103 (94.2%) | 0.1%, 95% CI: (-8.0%, 8.2%)

CI = confidence interval N = number of subjects

* Met pre-specified non-inferiority criterion (Margin used -15% and p<0.001, statistically significant at pre-specified alpha level of 0.01)

** Descriptive analysis of all subjects in the study including an overrun of subjects during the decision making at the interim analysis.

Mean (SD) baseline (i.e., within 3 hours prior to BALFAXAR or Kcentra infusion) INR was 3.96 (2.77) in the BALFAXAR group and 3.56 (1.82) in the Kcentra group. The proportion of patients achieving an INR ≤1.5 as measured 30 minutes after the end of the infusion was 78.1% in the BALFAXAR group versus 71.8% in the Kcentra group (proportion difference of 6.3%; 95% CI: 5.5%, 18.0%). Overall, 72.1% of patients had vitamin K administered, with a median dose of 10 mg in both groups (Table 8).

Table 8 Decrease of INR (to 1.5 or Less at 30 Minutes after End of Infusion) in Urgent Surgery RCT

Rating | No. (%) of subjects |  | Proportion difference BALFAXAR vs Kcentra (95% CI for difference)
 | BALFAXAR (N=105) | Kcentra (N=103)
Decrease of INR to ≤ 1.5 at 30 min | 82 (78.1) | 74 (71.8) | 6.3% (5.5%, 18.0%)

The median dose of BALFAXAR/ Kcentra was 25 IU of Factor IX/kg body weight in both treatment groups, ranging from 16 IU/kg to 50 IU/kg in the BALFAXAR group and 15 IU/kg to 50 IU/kg in the Kcentra group. The median duration of the infusion was 12 minutes in the BALFAXAR group (ranging from 8 to 50 minutes) and 13 minutes (ranging from 7 to 30 minutes) in the Kcentra group.

15 REFERENCES

1. Koehler M: Thrombogenicity of prothrombin complex concentrates. Thrombosis Research 1999;95:S13-S17.
2. Warkentin TE, Crowther MA: Reversing anticoagulants both old and new. Can.J. Anaesth. 2002;49:S11-S25.
3. Ansell J, Hirsh J, Poller L, et al: The pharmacology and management of the vitamin K antagonists: the Seventh ACCP Conference on Antithrombotic and Thrombolytic Therapy. Chest 2004;126:204S-233S.

16 HOW SUPPLIED/STORAGE AND HANDLING

BALFAXAR is supplied in single-dose vials.

Carton NDC Number | Container (Vial) NDC Number | Size | Color coding
68982-261-01 68982-261-02 | 68982-261-81 68982-261-82 | 500 IU Range FIX in 20 mL 1000 IU Range FIX in 40 mL | purple green

- BALFAXAR is supplied in a package with a single-dose vial of lyophilized powder and a vial of diluent (sterile Water for Injection), together with a transfer device.
- Components used in the packaging of BALFAXAR are not made with natural rubber latex.
- Store BALFAXAR for up to 36 months at 2°C to 25°C (36°F to 77°F) from the date of manufacture. Do not freeze.
- Do not use beyond the expiration date on the vial label and carton.
- Store the vial in the original package to protect it from light.
- Reconstitute the BALFAXAR powder only directly before use. Use the solution immediately after reconstitution. However, if it is not administered immediately, the reconstituted solution can be stored for up to 8 hours at room temperature (20°C to 25°C; 68°F to 77°F), provided sterility of the stored product is maintained. Discard partially used vials.

17 PATIENT COUNSELING INFORMATION

- Inform patients of the signs and symptoms of allergic hypersensitivity reactions, such as urticaria, rash, tightness of the chest, wheezing, hypotension and/or anaphylaxis experienced during or after injection of BALFAXAR. [ see Warnings and Precautions (5.1) ].
- Inform patients of signs and symptoms of thrombosis, such as limb or abdomen swelling and/or pain, chest pain or pressure, shortness of breath, loss of sensation or motor power, altered consciousness, vision, or speech. [ see Warnings and Precautions (5.2) ].
- Inform patients that, because BALFAXAR is made from human blood, it may carry a risk of transmitting infectious agents, e.g., viruses, the variant Creutzfeldt-Jakob disease (vCJD) agent, and theoretically, the Creutzfeldt-Jakob disease (CJD) agent. [ see Warnings and Precautions (5.3), Description (11) ].

Manufactured by:

Octapharma Pharmazeutika Produktionsges.m.b.H.

Oberlaaer Strasse 235

1100 Vienna, Austria

U.S. License No. 1646

Distributed by:

Octapharma USA Inc.

117 W Century Road

Paramus, NJ 07652

PACKAGE LABEL - PRINCIPAL DISPLAY PANEL

Prothrombin Complex Concentrate (Human)

BALFAXAR

500 IU Range FIX in 20 mL

NDC 68982-261-01

BALFAXAR

1000 IU Range FIX in 40 mL

NDC 68982-261-01